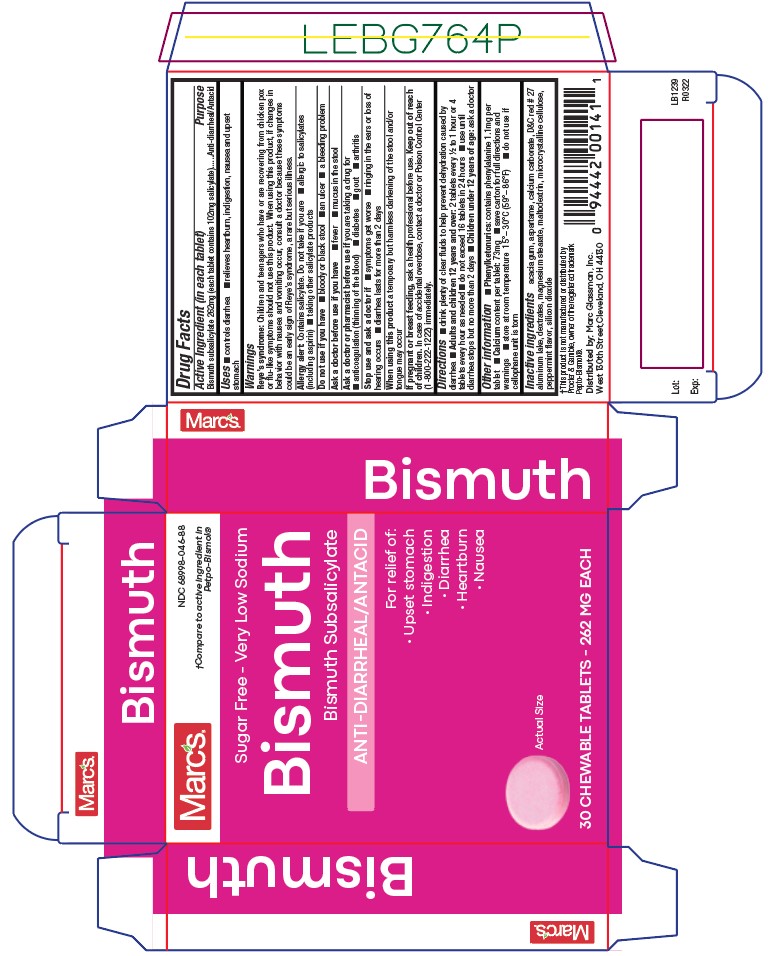 DRUG LABEL: Bismuth Chewable
NDC: 68998-046 | Form: TABLET, CHEWABLE
Manufacturer: Marc Glassman, Inc.
Category: otc | Type: HUMAN OTC DRUG LABEL
Date: 20161219

ACTIVE INGREDIENTS: BISMUTH SUBSALICYLATE 262 mg/1 1
INACTIVE INGREDIENTS: ASPARTAME; CALCIUM CARBONATE; D&C RED NO. 27; DEXTRATES; MAGNESIUM STEARATE; MALTODEXTRIN; MICROCRYSTALLINE CELLULOSE; SILICON DIOXIDE

046 - Bismuth

Active ingredient

Bismuth subsalicylate 262mg (each tablet contains 102mg salicylate)

Purpose

Antidiarrheal/Antacid

Uses

■ controls diarrhea

■ relieves heartburn, indigestion, nausea and upset stomach

Warnings

Reye’s syndrome: Children and teenagers who have or are recovering from chicken pox or flu-like symptoms should not use this product. When using this product, if changes in behavior with nausea and vomiting occur, consult a doctor because these symptoms could be an early sign of Reye’s syndrome, a rare but serious illness.

Allergy alert: Contains salicylate. Do not take if you are

■ allergic to salicylates (including aspirin)

■ taking other salicylate products

Do not use if you have

■ bloody or black stool

■ an ulcer

■ a bleeding problem

Ask a doctor before use if you have

■ fever

■ mucus in the stool

Ask a doctor or pharmacist before use if

you are taking a drug for

■ anticoagulation (thinning of the blood)

■ diabetes

■ gout

■ arthritis

When using this product

a temporary but harmless darkening of the stool and/or tongue may occur

Stop use and ask a doctor if

■ symptoms get worse

■ ringing in the ears or loss of hearing occurs

■ diarrhea lasts for more than 2 days

Pregnancy/Breastfeeding

ask a health professional before use.

Keep out of reach of children

In case of accidental overdose, contact a doctor or Poison Control Center (1-800-222-1222) immediately.

Directions

■ drink plenty of clear fluids to help revent deydration caused by diarrhea

■ Adults and children 12 years and over: 2 tablets every ½ to 1 hour or 4 tablets every hour as needed

■ do not exceed 16 tablets in 24 hours

■ use until diarrhea stops but no more than 2 days

■ Children under 12 years of age: ask a doctor

Other information

■ Phenylketonurics: contains phenylalanine 1.1mg per tablet

■ Calcium content per tablet: 73mg

■ save carton for full directions and warnings

■ store at room temperature 15°– 30°C (59°– 86°F)

■ do not use if cellophane unit is torn

Inactive ingredients

acacia gum, aspartame, calcium carbonate, D&C red # 27 aluminum lake, dextrates, magnesium stearate, maltodextrin, microcrystalline cellulose, peppermint flavor, silicon dioxide

Principal Display Panel

Bismuth